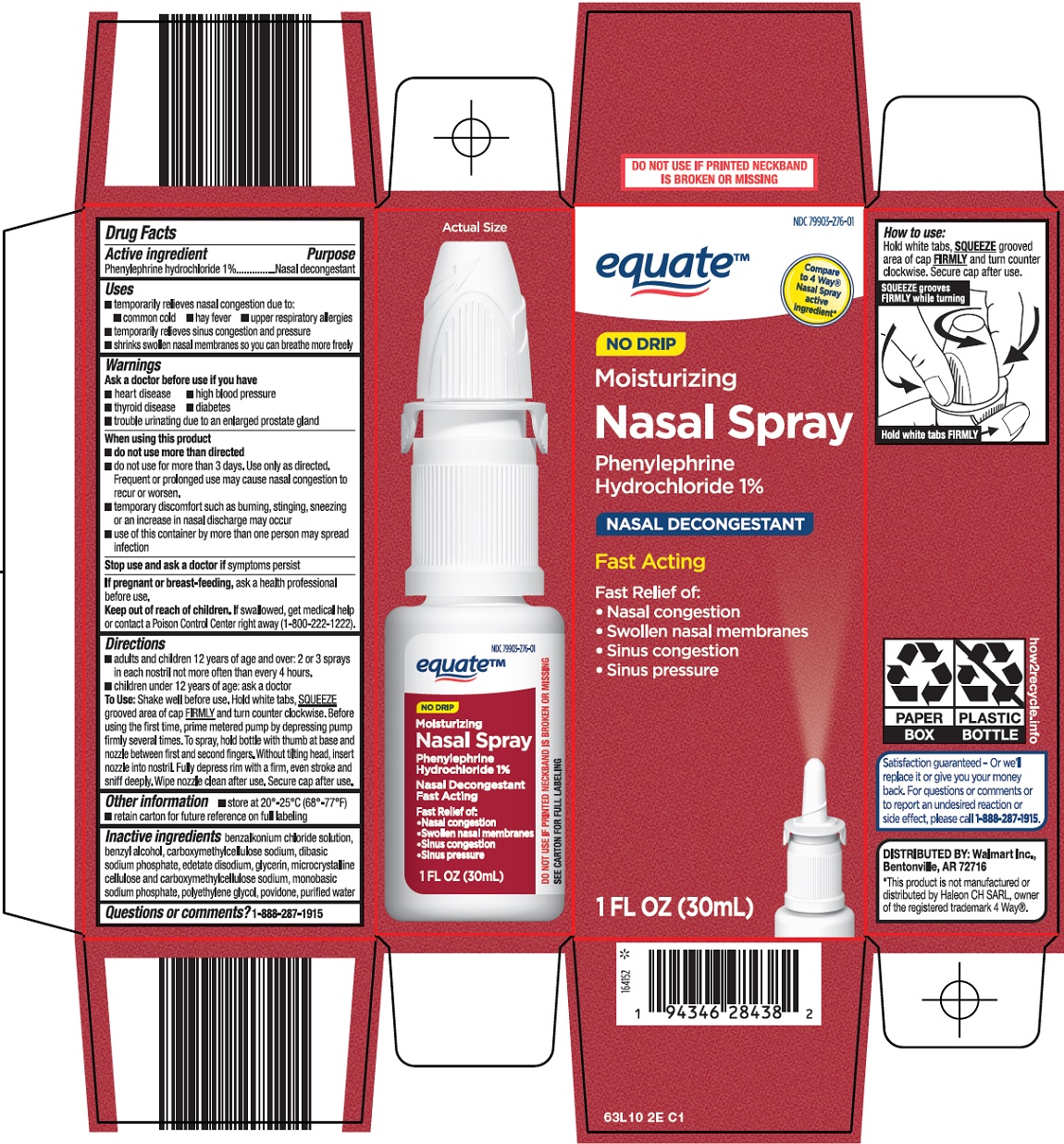 DRUG LABEL: Equate Nasal
NDC: 79903-276 | Form: SPRAY
Manufacturer: WALMART INC.
Category: otc | Type: HUMAN OTC DRUG LABEL
Date: 20250210

ACTIVE INGREDIENTS: PHENYLEPHRINE HYDROCHLORIDE 10 mg/1 mL
INACTIVE INGREDIENTS: BENZALKONIUM CHLORIDE; BENZYL ALCOHOL; CARBOXYMETHYLCELLULOSE SODIUM, UNSPECIFIED; SODIUM PHOSPHATE, DIBASIC, UNSPECIFIED FORM; EDETATE DISODIUM; GLYCERIN; MICROCRYSTALLINE CELLULOSE; SODIUM PHOSPHATE, MONOBASIC, UNSPECIFIED FORM; POLYETHYLENE GLYCOL, UNSPECIFIED; POVIDONE, UNSPECIFIED; WATER

Wal-Mart Nasal Spray Drug Facts

Active ingredient

Phenylephrine hydrochloride 1%

Purpose

Nasal decongestant

Uses

- temporarily relieves nasal congestion due to:
- common cold
- hay fever
- upper respiratory allergies
- temporarily relieves sinus congestion and pressure
- shrinks swollen nasal membranes so you can breathe more freely

Warnings

Ask a doctor before use if you have

- heart disease
- high blood pressure
- thyroid disease
- diabetes
- trouble urinating due to an enlarged prostate gland

When using this product

- do not use more than directed
- do not use for more than 3 days. Use only as directed. Frequent or prolonged use may cause nasal congestion to recur or worsen.
- temporary discomfort such as burning, stinging, sneezing or an increase in nasal discharge may occur
- use of this container by more than one person may spread infection

Stop use and ask a doctor if

symptoms persist

If pregnant or breast-feeding,

ask a health professional before use.

Keep out of reach of children.

If swallowed, get medical help or contact a Poison Control Center right away (1-800-222-1222).

Directions

- adults and children 12 years of age and over: 2 or 3 sprays in each nostril not more often than every 4 hours.
- children under 12 years of age: ask a doctor

To Use: Shake well before use. Hold white tabs, SQUEEZE grooved area of cap FIRMLY and turn counter clockwise. Before using the first time, prime metered pump by depressing pump firmly several times. To spray, hold bottle with thumb at base and nozzle between first and second fingers. Without tilting head, insert nozzle into nostril. Fully depress rim with a firm, even stroke and sniff deeply. Wipe nozzle clean after use. Secure cap after use.

Other information

- store at 20°-25°C (68°-77°F)
- retain carton for future reference on full labeling

Inactive ingredients

benzalkonium chloride solution, benzyl alcohol, carboxymethylcellulose sodium, dibasic sodium phosphate, edetate disodium, glycerin, microcrystalline cellulose and carboxymethylcellulose sodium, monobasic sodium phosphate, polyethylene glycol, povidone, purified water

Questions or comments?

1-888-287-1915

Package/Label Principal Display Panel

equate™

Compare to 4 Way® Nasal Spray active ingredient

NO DRIP

Moisturizing

Nasal Spray

Phenylephrine Hydrochloride 1%

Nasal Decongestant

Fast Acting

Fast Relief of:

Nasal congestion

Swollen nasal membranes

Sinus congestion

Sinus pressure

1 FL OZ (30mL)